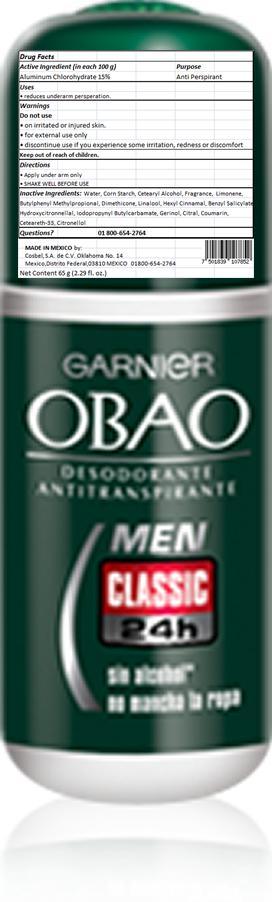 DRUG LABEL: Obao
NDC: 51769-412 | Form: STICK
Manufacturer: ALL NATURAL DYNAMICS
Category: otc | Type: HUMAN OTC DRUG LABEL
Date: 20130830

ACTIVE INGREDIENTS: Aluminum Chlorohydrate 15 g/100 g
INACTIVE INGREDIENTS: Water; STARCH, CORN; CETOSTEARYL ALCOHOL; IODOPROPYNYL BUTYLCARBAMATE; DIMETHICONE; LINALOOL, (+/-)-; .ALPHA.-HEXYLCINNAMALDEHYDE; CETEARETH-33; .BETA.-CITRONELLOL, (R)-; BENZYL SALICYLATE; CITRAL; COUMARIN; Butylphenyl Methylpropional

OBAO Sensitive Passion

Warnings:

For External Use Only. Do Not Apply On Irritated Or Injured Skin. Discontinue Use If You Experience Some Irritation, Redness Or Discomfort.

Active Ingredient:

Aluminum Chlorohydrate 15%

Purpose

Anti Perspirant

Keep Out Of The Reach Of Children

USE:

reduces underarm persperation

Directions:

Apply under arm only.

SHAKE WELL BEFORE USE.

Inactive Ingredients:

Water, Corn Starch, Cetearyl Alcohol, Fragrance, Iodopropynyl butylcarbamate, Dimethicone, Bambusa Vulgaris Extract, Linalool, Caprylic/capric triglyceride, Ceteareth-33, Citronellol , FIL: C26181/1